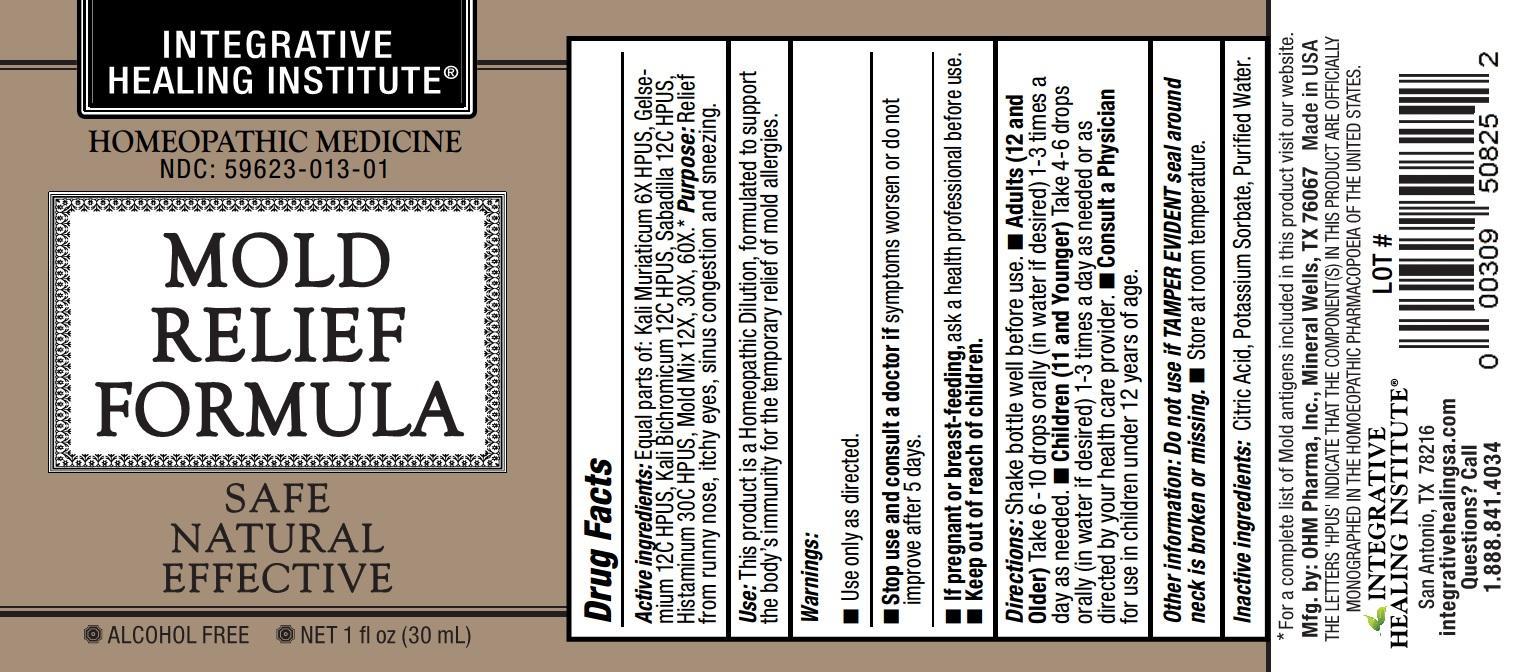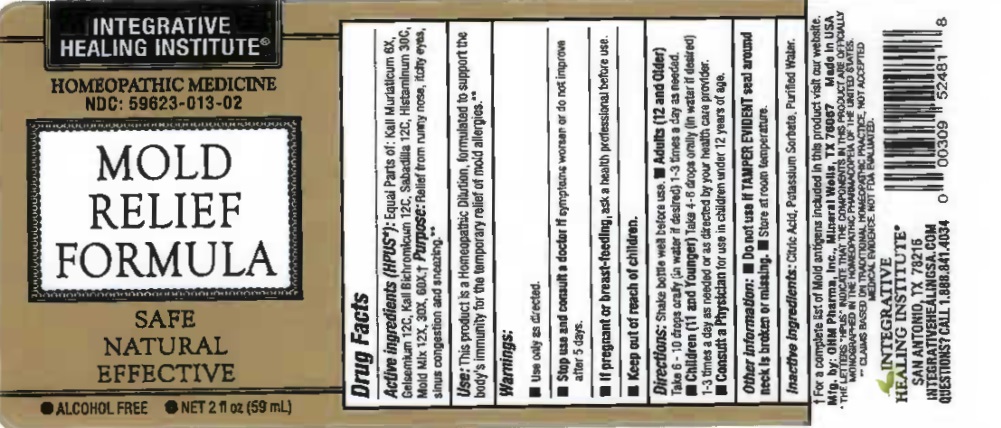 DRUG LABEL: Mold Relief Formula

NDC: 59623-013 | Form: LIQUID
Manufacturer: Integrative Healing Institute, LLC
Category: homeopathic | Type: HUMAN OTC DRUG LABEL
Date: 20251017

ACTIVE INGREDIENTS: POTASSIUM CHLORIDE 6 [hp_X]/1 mL; GELSEMIUM SEMPERVIRENS ROOT 12 [hp_C]/1 mL; POTASSIUM DICHROMATE 12 [hp_C]/1 mL; SCHOENOCAULON OFFICINALE SEED 12 [hp_C]/1 mL; HISTAMINE DIHYDROCHLORIDE 30 [hp_C]/1 mL; ALTERNARIA ALTERNATA 12 [hp_X]/1 mL; ASPERGILLUS FUMIGATUS 12 [hp_X]/1 mL; ASPERGILLUS NIGER VAR. NIGER 12 [hp_X]/1 mL; BOLETUS SATANAS FRUITING BODY 12 [hp_X]/1 mL; BOTRYTIS CINEREA 12 [hp_X]/1 mL; CANDIDA ALBICANS 12 [hp_X]/1 mL; PASSALORA FULVA 12 [hp_X]/1 mL; FUSARIUM OXYSPORUM 12 [hp_X]/1 mL; COCHLIOBOLUS SATIVUS 12 [hp_X]/1 mL; RHIZOPUS STOLONIFER 12 [hp_X]/1 mL; AUREOBASIDIUM PULLULANS VAR. PULLUTANS 12 [hp_X]/1 mL; USTILAGO MAYDIS 12 [hp_X]/1 mL
INACTIVE INGREDIENTS: WATER; POTASSIUM SORBATE; CITRIC ACID MONOHYDRATE

MOLD RELIEF FORMULA

ACTIVE INGREDIENT

Active ingredients:Equal parts of: Kali Muriaticum 6X HPUS, Gelsemium 12C HPUS, Kali Bichromicum 12C HPUS, Sabadilla 12C HPUS, Histaminum 30C HPUS, Mold Mix 12X, 30X, 60X.*

PURPOSE

Purpose:Relief from runny nose, itchy eyes, sinus congestion and sneezing.

INDICATIONS AND USAGE

Use:This product is a Homeopathic Dilution, formulated to support the body's immunity for the temporary relief of mold allergies.

Warnings:

- Use only as directed.
- Stop use and consult a doctor ifsymptoms worsen or do not improve after 5 days.
- If pregnant or breast-feeding,ask a health professional before use.

- Keep out of reach of children.

DOSAGE AND ADMINISTRATION

Directions:Shake bottle well before use.

- Adults (12 and Older)Take 6-10 drops orally (in water if desired) 1-3 times a day as needed.
- Children (11 and Younger)Take 4-6 drops orally (in water if desired) 1-3 times a day as needed or as directed by your health care provider.
- Consult a Physicianfor use in children under 12 years of age.

Other information: Do not use if TAMPER EVIDENT seal around neck is broken or missing.

- Store at room temperature.

Inactive ingredients:Citric Acid, Potassium Sorbate, Purified Water.

OTHER SAFETY INFORMATION

* For a complete list of Mold antigens included in this product visit our website.

Mfg. by: OHM Pharma, Inc., Mineral Wells, TX 76067
Made in USA

THE LETTERS 'HPUS' INDICATE THAT THE COMPONENT(S) IN THIS PRODUCT ARE OFFICIALLY MONOGRAPHED IN THE HOMOEOPATHIC PHARMACOPOEIA OF THE UNITED STATES.

QUESTIONS

INTEGRATIVE HEALING INSTITUTE®

San Antonio, TX 78216
integrativehealingsa.com
Questions?Call 1.888.841.4034

PACKAGE LABEL

INTEGRATIVE HEALING INSTITUTE®

HOMEOPATHIC MEDICINE

- NDC: 59623-013-01

MOLD RELIEF FORMULA

- SAFE
- NATURAL
- EFFECTIVE

- ALCOHOL FREE
- NET 1 fl oz (30 mL)

INTEGRATIVE HEALING INSTITUTE

HOMEOPATHIC MEDICINE

NDC: 59623-013-02

MOLD RELIEF FORMULA

SAFE
NATURAL
EFFECTIVE

ALCOHOL FREE
NET 2 fl oz (59 mL)